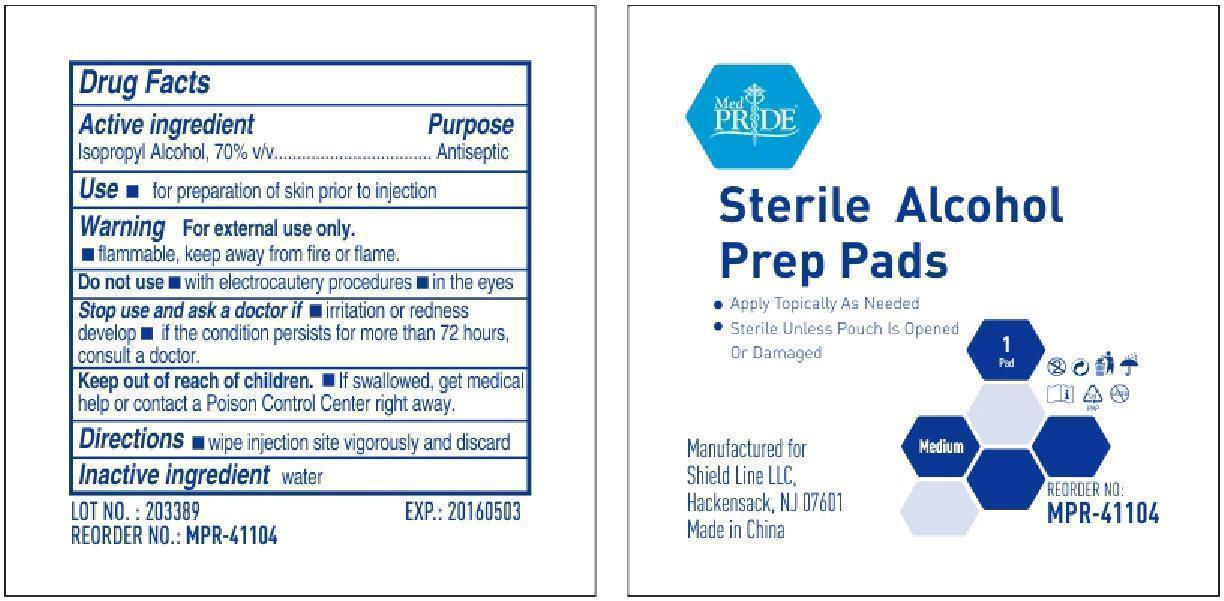 DRUG LABEL: MedPride
NDC: 52410-4110 | Form: CLOTH
Manufacturer: Shield Line LLC
Category: otc | Type: HUMAN OTC DRUG LABEL
Date: 20250820

ACTIVE INGREDIENTS: ISOPROPYL ALCOHOL 0.7 g/1 1
INACTIVE INGREDIENTS: WATER

Drug Facts

Active Ingredient

Isopropyl Alcohol 70% v/v

Purpose

Antiseptic

Uses

■ for preparation of skin prior to injection

Warnings

For external use only
■ flammable, keep away from fire or flame

Do not use

■ with electrocautery procedures ■ in the eyes

Stop use and ask a doctor if

■if irritation and redness develops ■ if condition persist for more than 72 hours consult a doctor.

Keep out of reach of children. If swallowed contact a doctor or Poison Control Center right away.

Directions

■wipe the injection site vigorously and discard

Inactive Ingredient

water